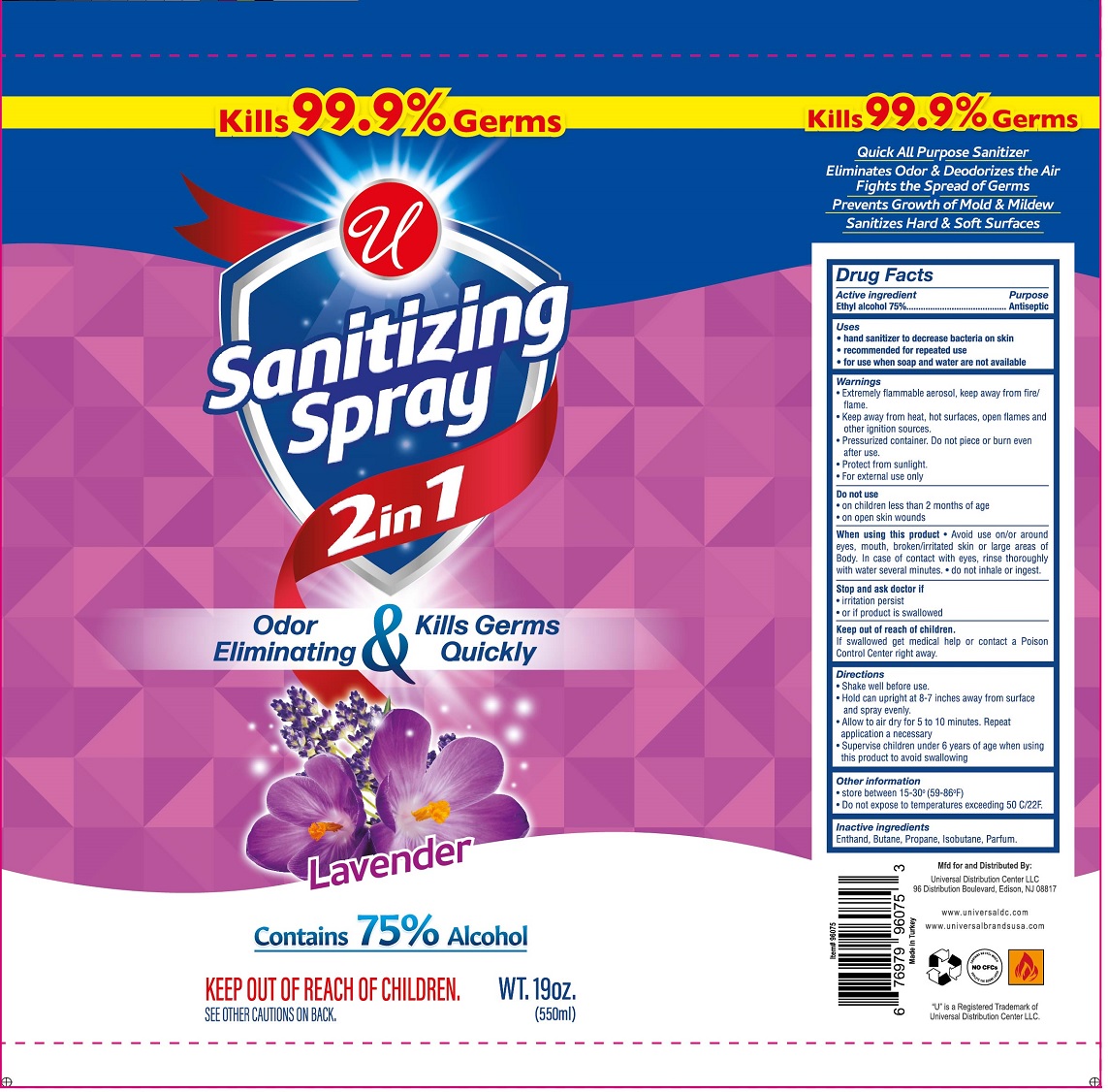 DRUG LABEL: UNIVERSAL SANITIZING LAVENDER
NDC: 52000-403 | Form: AEROSOL, SPRAY
Manufacturer: Universal Distribution Center Llc
Category: otc | Type: HUMAN OTC DRUG LABEL
Date: 20210209

ACTIVE INGREDIENTS: ALCOHOL 75 mL/100 mL
INACTIVE INGREDIENTS: BUTANE; PROPANE; ISOBUTANE

Universal Sanitizing Spray Lavender

Active ingredient

Ethyl alcohol 75%

Purpose

Antiseptic

Uses

• hand sanitizer to decrease bacteria on skin

• recommended for repeated use

• for use when soap and water are not available

Warnings

• Extremely flammable aerosol, keep away from fire/flame.

• Keep away from heat, hot surfaces, open flames and other ignition sources.

• Pressurized container. Do not piece or burn even after use.

• Protect from sunlight.

• For external use only

Do not use

• on children less than 2 months of age

• on open skin wounds

When using this product • Avoid use on/or around eyes, mouth, broken/irritated skin or large areas of Body. In case of contact with eyes, rinse thoroughly with water several minutes. • do not inhale or ingest.

Stop and ask doctor if

• irritation persist

• or if product is swallowed

Keep out of reach of children.

If swallowed get medical help or contact a Poison Control Center right away.

Directions

• Shake well before use.

• Hold can upright at 8-7 inches away from surface and spray evenly.

• Allow to air dry for 5 to 10 minutes. Repeat application as necessary

• Supervise children under 6 years of age when using this product to avoid swallowing

Other information

• store between 15-30° (59-86°F)

• Do not expose to temperatures exceeding 50 C/22F.

Inactive ingredients

Butane, Propane, Isobutane, Parfum.

Kills 99.9% Germs

2 in 1

Odor Eliminating & Kills Germs Quickly

Contains 75% Alcohol

KEEP OUT OF REACH OF CHILDREN.

Quick All Purpose Sanitizer

Eliminates Odor & Deodorizes the Air

Fights the Spread of Germs

Prevents Growth of Mold & Mildew

Sanitizes Hard & Soft Surfaces

Mfd for and Distributed By:

Universal Distribution Center LLC

96 Distribution Boulevard, Edison, NJ 08817

Made in Turkey

www.universaldc.com

www.universalbrandsusa.com

NO CFCs

CONTAINS NO CFCs WHICH DEPLETE THE OZONE LAYER

"U" is a Registered Trademark of Universal Distribution Center LLC.